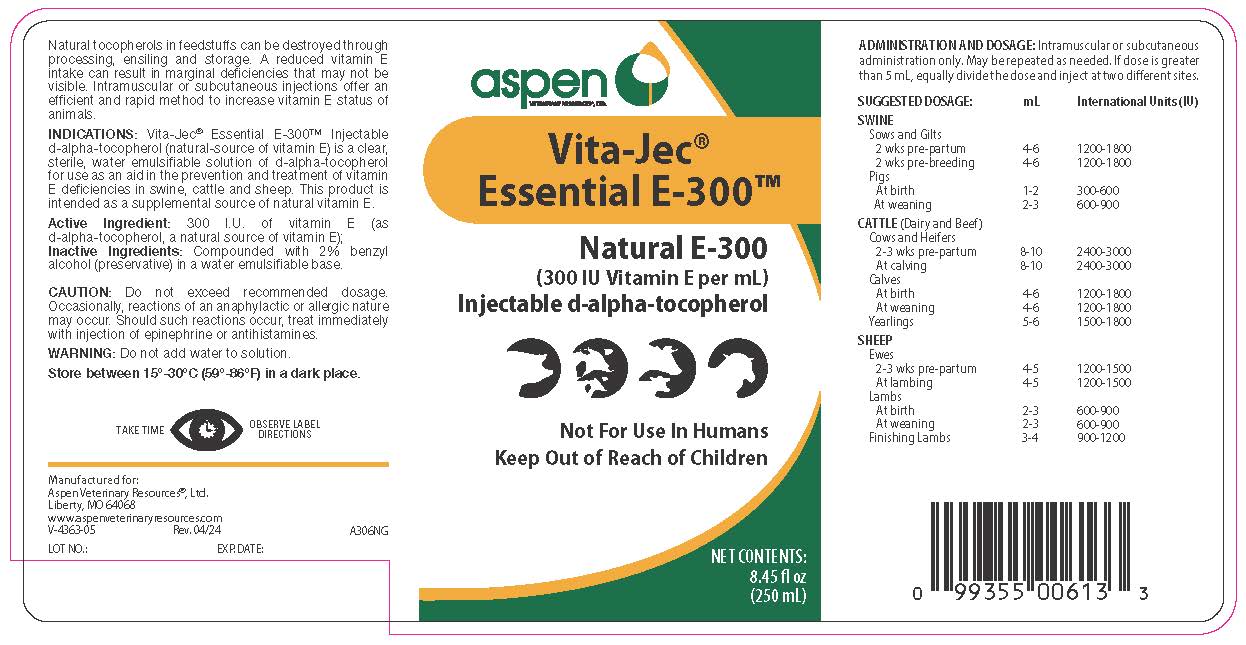 DRUG LABEL: Vita-Jec Essential E-300
NDC: 46066-236 | Form: INJECTION
Manufacturer: Aspen Veterinary Resources, Ltd
Category: animal | Type: OTC ANIMAL DRUG LABEL
Date: 20240603

ACTIVE INGREDIENTS: ALPHA-TOCOPHEROL 201 mg/1 mL

Vita-Jec Essential E-300

PURPOSE

Natural E-300

(300 IU Vitamin E per mL)

Injectable d-alpha-tocopherol

Not For Use In Humans

Keep Out of Reach of Children

Natural tocopherols in feedstuffs can be destroyed through processing, ensiling and storage. A reduced vitamin E intake can result in marginal deficiencies that may not be visible. Intramuscular or subcutaneous injection offer an efficient and rapid method to increase vitamin E status of animals.

INDICATIONS

Vita-Jec Essential E-300 Injectable d-alpha-tocopherol (natural-source vitamin E) is a clear, sterile, water emulsifiable solution of d-alpha-tocopherol for use as an aid in the prevention and treatment of vitamin E deficiencies in swine, cattle and sheep. This product is intended as a supplemental source of natural vitamin E.

Active Ingredient: 300 I.U. of vitamin E (as
d-alpha-tocopherol, a natural source of vitamin E);
Inactive Ingredients: Compounded with 2% benzyl
alcohol (preservative) in a water emulsifiable base.

CAUTION

Do not exceed recommended dosage. Occasionally, reactions of an anaphylactic or allergic nature may occur. Should such reactions occur, treat immediately with injection of epinephrine or antihistamines.

WARNING

Do not add water to solution.

STORAGE AND HANDLING

Store between 15° and 30°C (59°-86°F) in a dark place.

TAKE TIME OBSERVE LABEL DIRECTIONS

ADMINISTRATION AND DOSAGE

Intramuscular or subcutaneous administration only. May be repeated as needed. If dose is greater than 5 mL, equally divide the dose and inject at two different sites.

SUGGESTED DOSAGE |  | International
 | mL | Units
SWINE
Sows and Gilts
2 wks pre-partum | 4-6 | 1200-1800
2 wks pre-breeding | 4-6 | 1200-1800
Pigs
At birth | 1-2 | 300-600
At weaning | 2-3 | 600-900
CATTLE (Dairy and Beef)
Cows and Heifers
2-3 wks pre -partum | 8-10 | 2400-3000
At calving | 8-10 | 2400-3000
Calves
At birth | 4-6 | 1200-1800
At weaning | 4-6 | 1200-1800
Yearlings | 5-6 | 1500-1800
SHEEP
Ewes
2-3 wks pre-partum | 4-5 | 1200-1500
At lambing | 4-5 | 1200-1500
Lambs
At birth | 2-3 | 600-900
At weaning | 2-3 | 600-900
Finishing Lambs | 3-4 | 900-1200